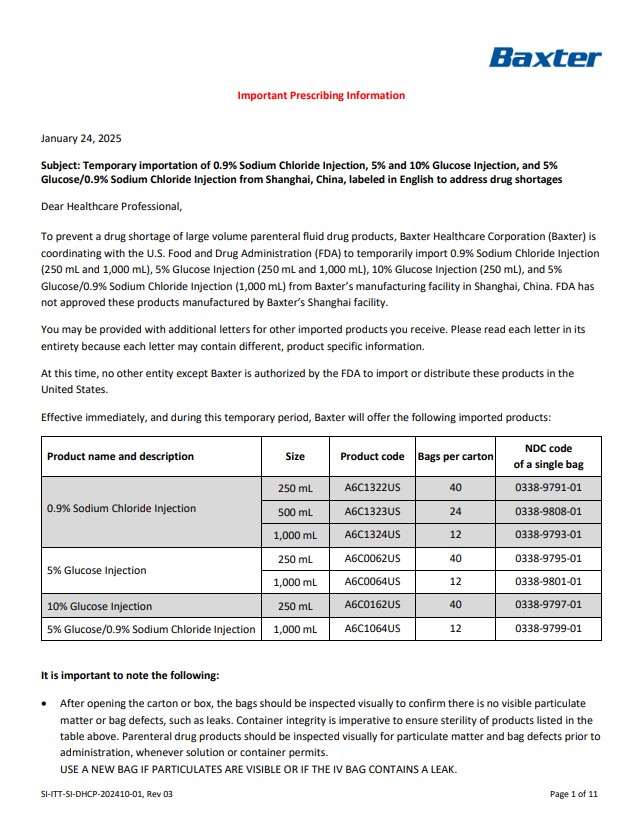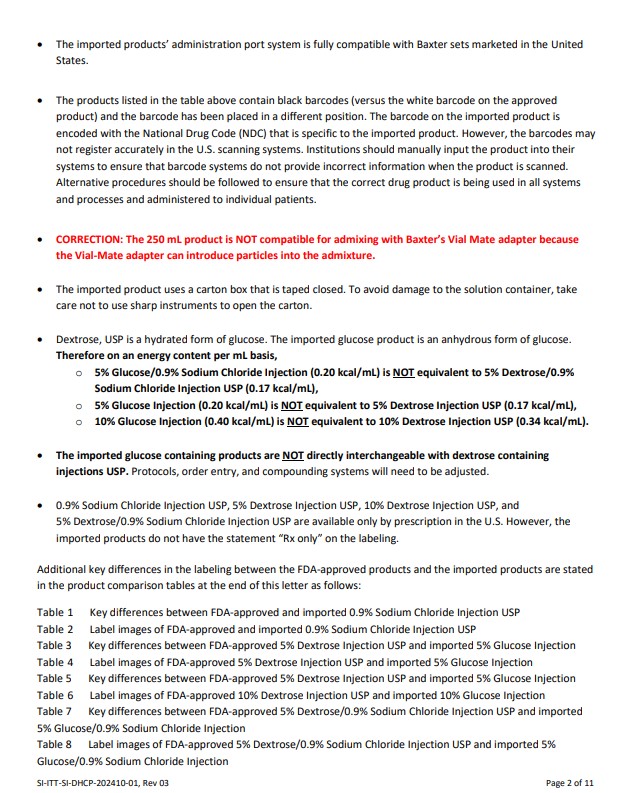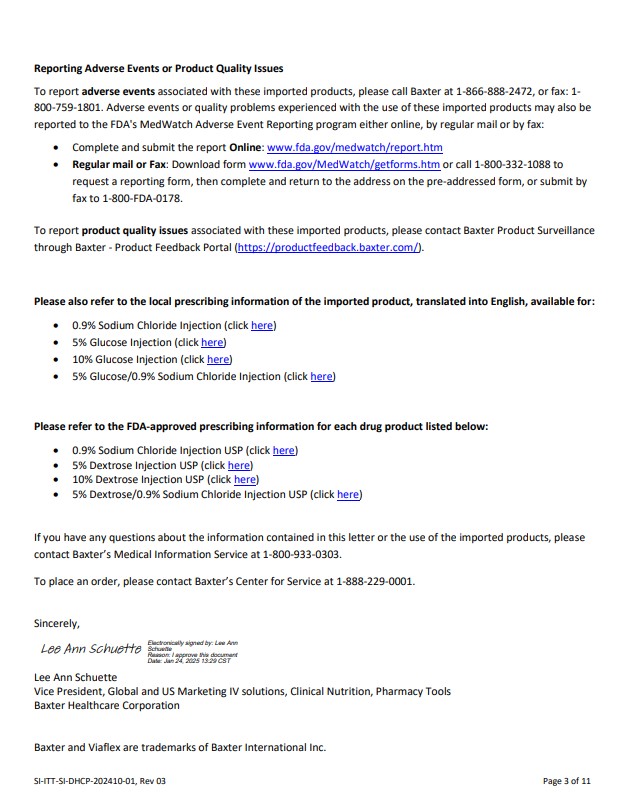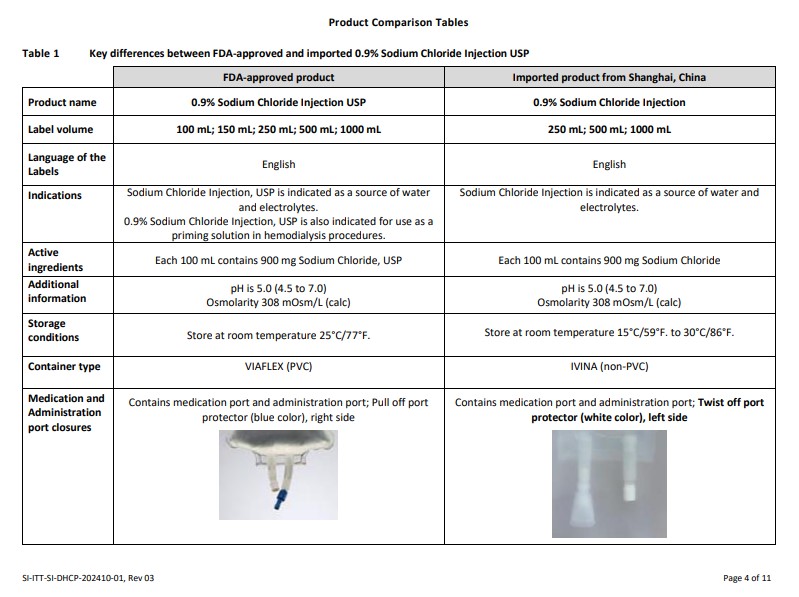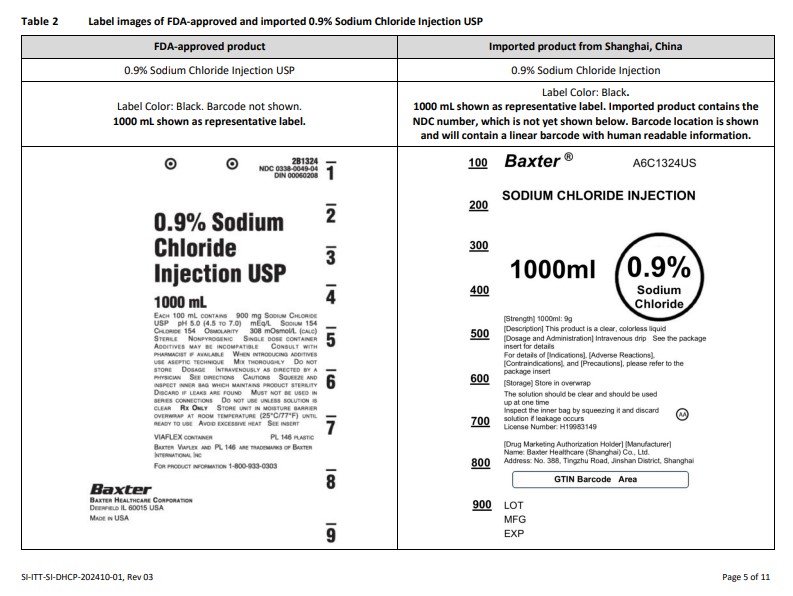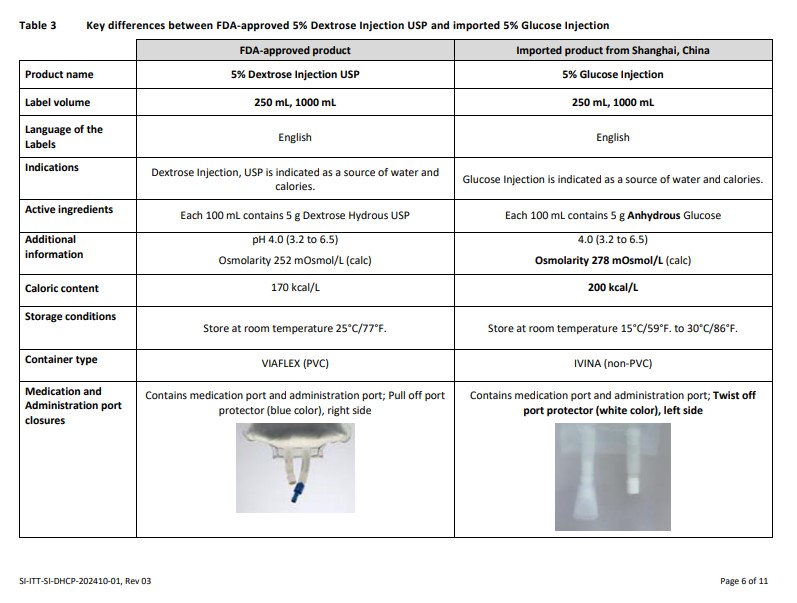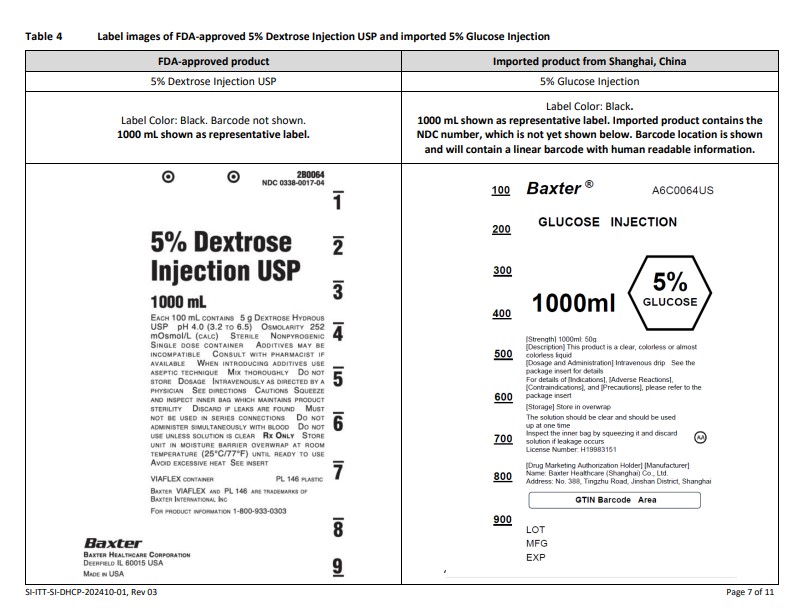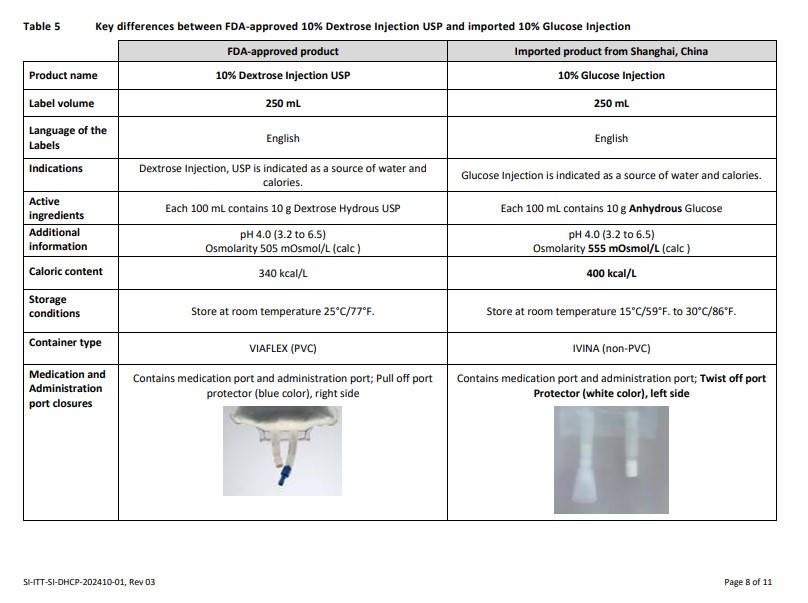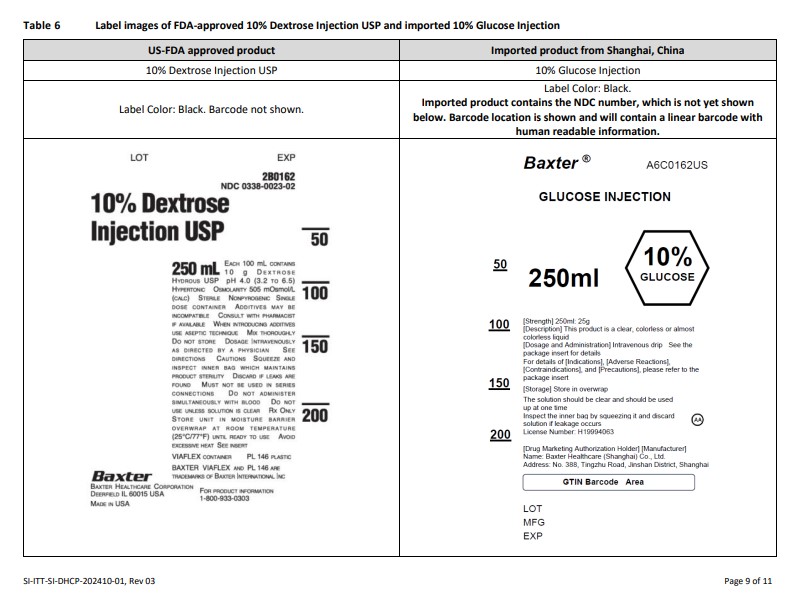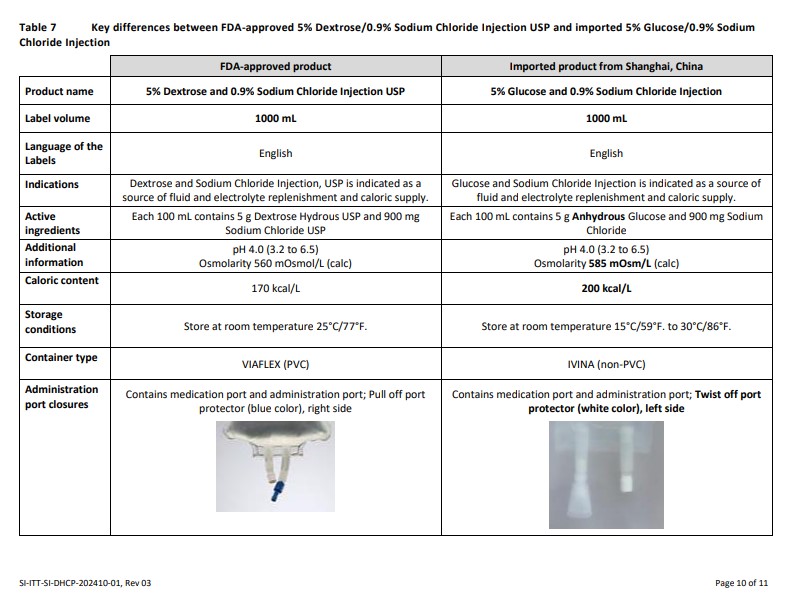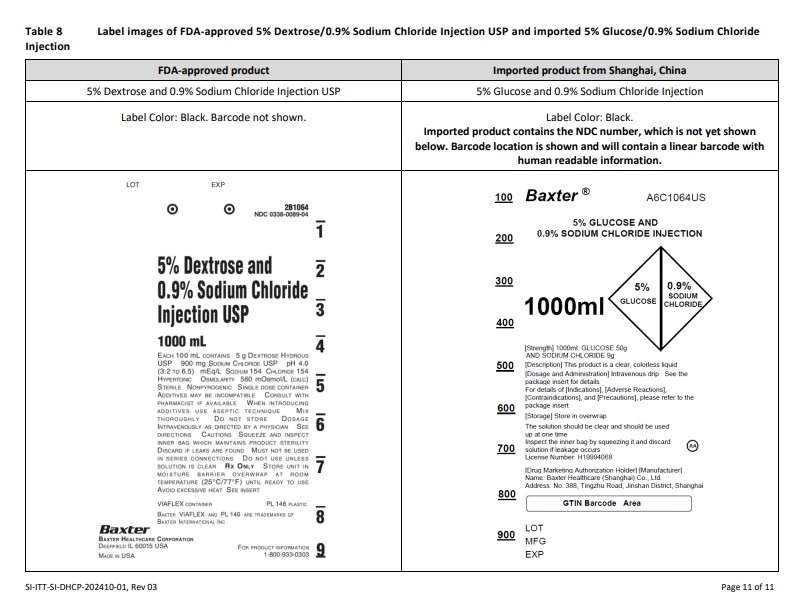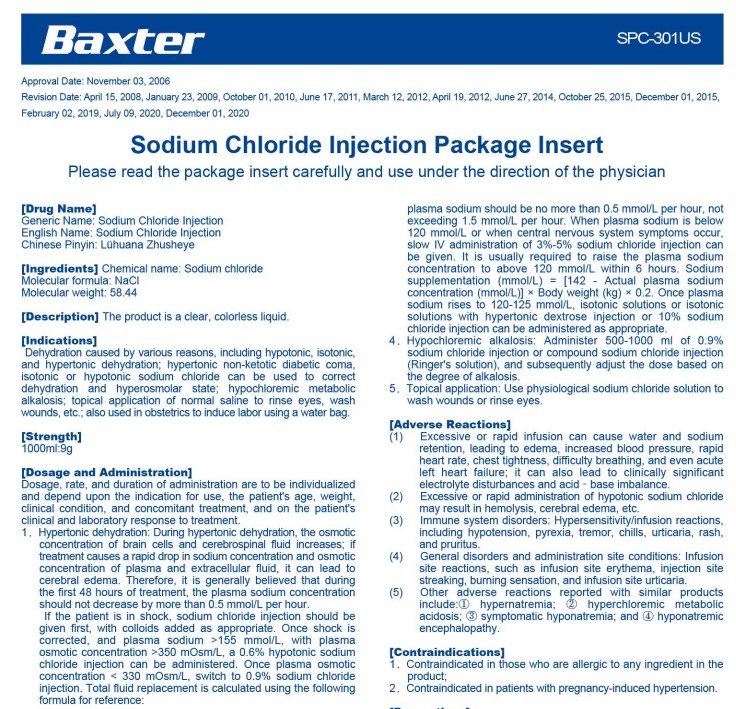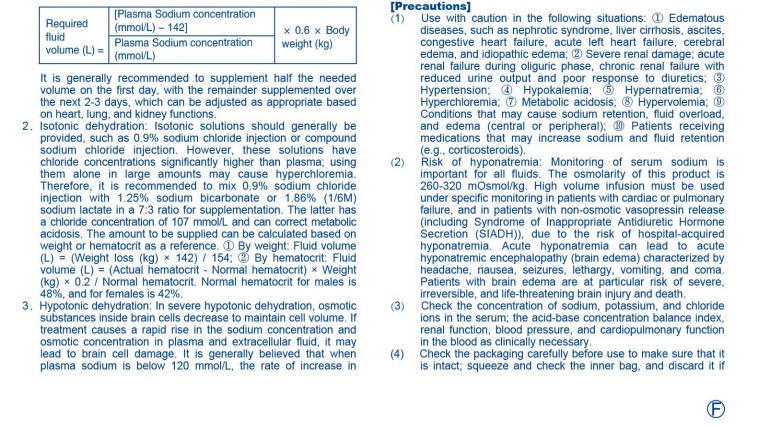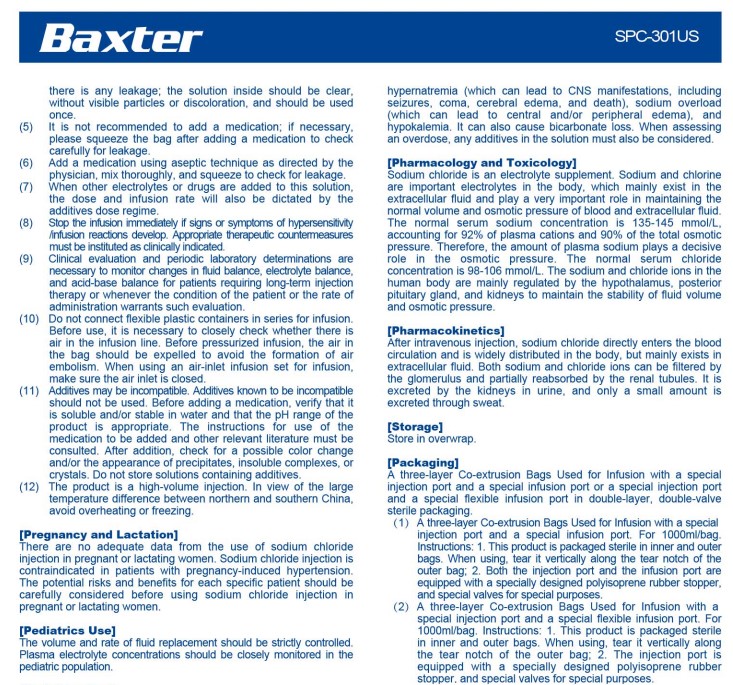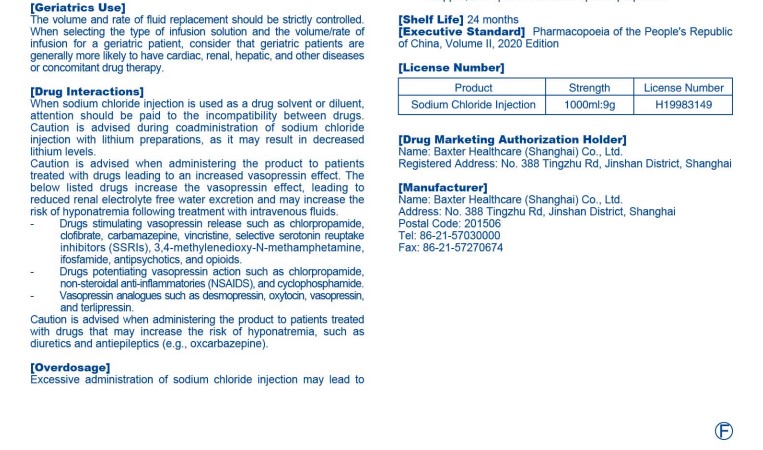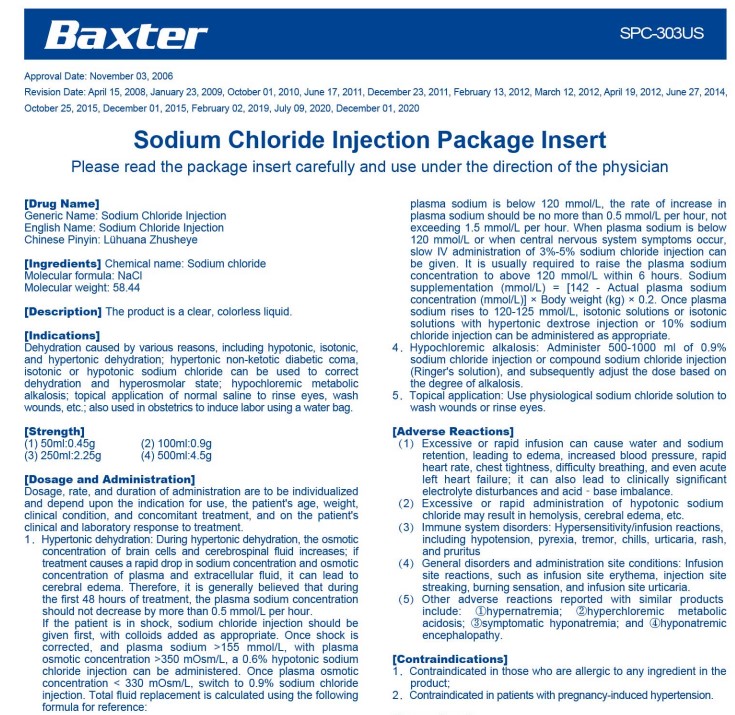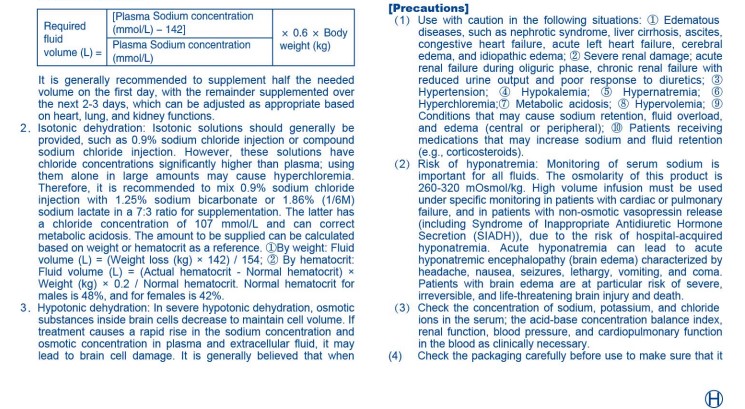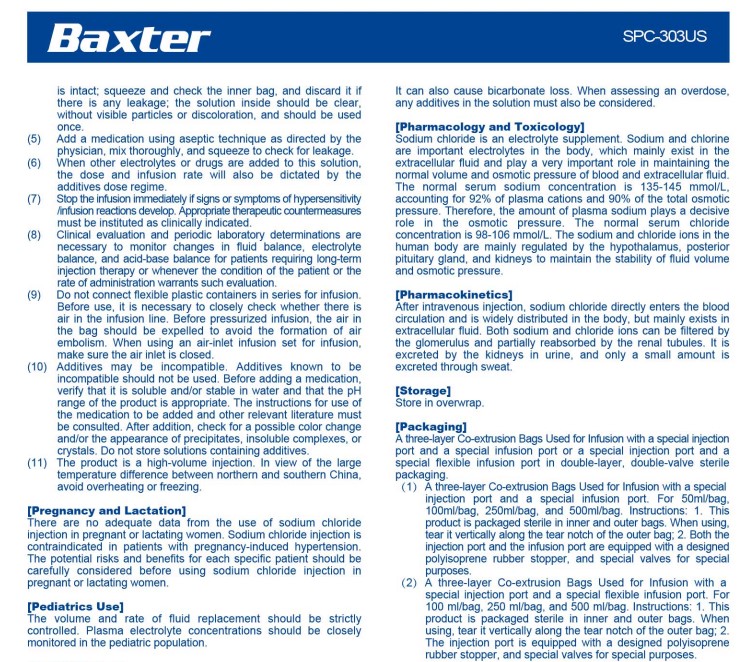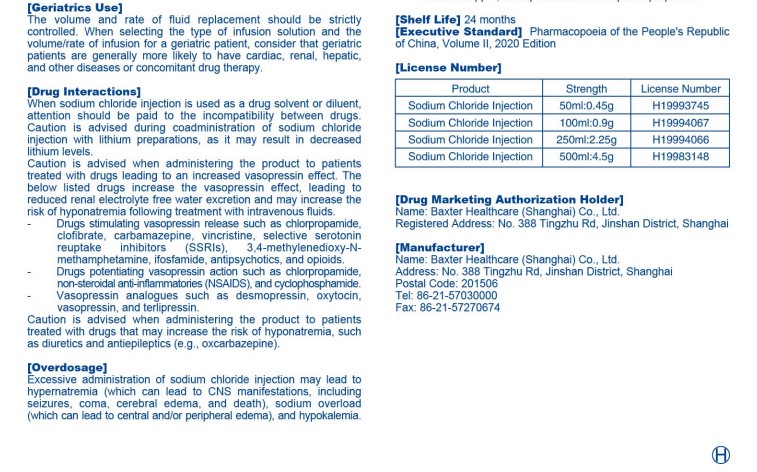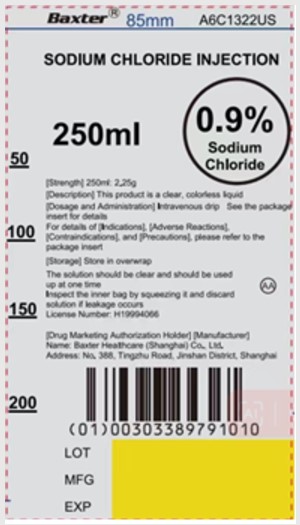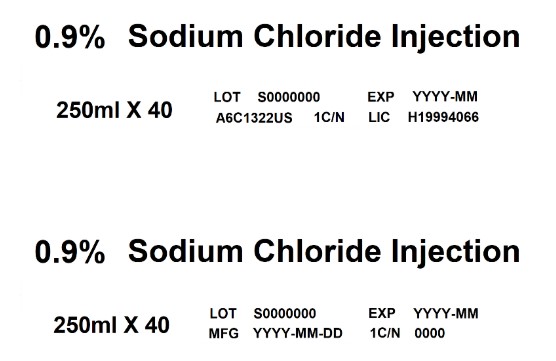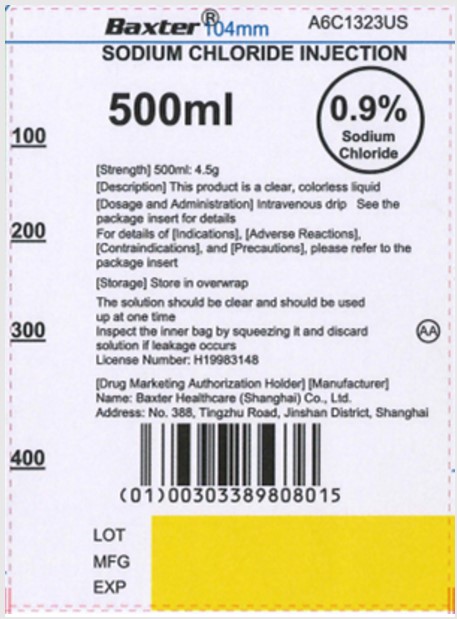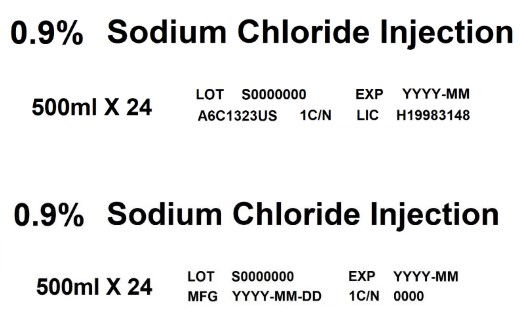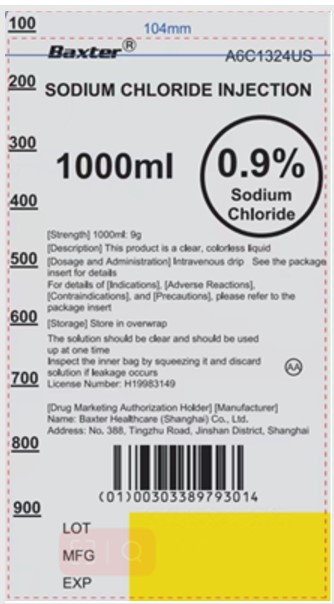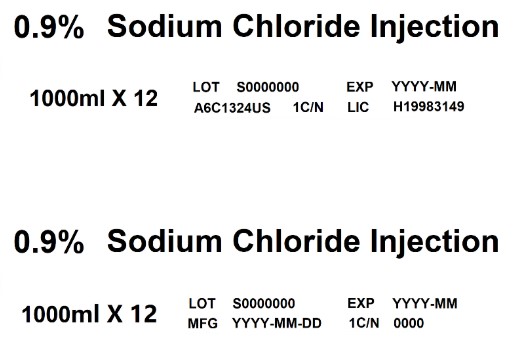 DRUG LABEL: Sodium Chloride
NDC: 0338-9791 | Form: INJECTION, SOLUTION
Manufacturer: Baxter Healthcare Corporation
Category: prescription | Type: HUMAN PRESCRIPTION DRUG LABEL
Date: 20250124

ACTIVE INGREDIENTS: SODIUM CHLORIDE 9 g/1000 mL
INACTIVE INGREDIENTS: WATER

0.9% SODIUM CHLORIDE INJECTION

HEALTH CARE PROFESSIONAL LETTER

Reporting Adverse Events or Product Quality Issues
To report adverse events associated with these imported products, please call Baxter at 1-866-888-2472, or fax: 1- 800-759-1801. Adverse events or quality problems experienced with the use of these imported products may also be reported to the FDA's MedWatch Adverse Event Reporting program either online, by regular mail or by fax:
• Complete and submit the report Online: www.fda.gov/medwatch/report.htm
• Regular mail or Fax: Download form www.fda.gov/MedWatch/getforms.htm or call 1-800-332-1088 to request a reporting form, then complete and return to the address on the pre-addressed form, or submit by fax to 1-800-FDA-0178.

To report product quality issues associated with these imported products, please contact Baxter Product Surveillance through Baxter - Product Feedback Portal (https://productfeedback.baxter.com/).

Please also refer to the local prescribing information of the imported product, translated into English, available for:
• 0.9% Sodium Chloride Injection (click https://nctr-crs.fda.gov/fdalabel/ui/spl-summaries/criteria/723233)
• 5% Glucose Injection (click https://nctr-crs.fda.gov/fdalabel/ui/spl-summaries/criteria/723235)
• 10% Glucose Injection (click https://nctr-crs.fda.gov/fdalabel/ui/spl-summaries/criteria/723237)
• 5% Glucose/0.9% Sodium Chloride Injection (click https://nctr-crs.fda.gov/fdalabel/ui/spl-summaries/criteria/723238)

Please refer to the FDA-approved prescribing information for each drug product listed below:
• 0.9% Sodium Chloride Injection USP (click https://www.dailymed.nlm.nih.gov/dailymed/getFile.cfm?setid=f55bd888-5e01-474d-871b-24654c070178&type=pdf&name=f55bd888-5e01-474d-871b-24654c070178)
• 5% Dextrose Injection USP (click https://www.dailymed.nlm.nih.gov/dailymed/getFile.cfm?setid=3bb406a9-f5cb-403a-b1bb-5c4facbea3d5&type=pdf&name=3bb406a9-f5cb-403a-b1bb-5c4facbea3d5)
• 10% Dextrose Injection USP (click https://www.dailymed.nlm.nih.gov/dailymed/getFile.cfm?setid=3bb406a9-f5cb-403a-b1bb-5c4facbea3d5&type=pdf&name=3bb406a9-f5cb-403a-b1bb-5c4facbea3d5)
• 5% Dextrose/0.9% Sodium Chloride Injection USP (click https://www.accessdata.fda.gov/drugsatfda_docs/label/2019/016678s007,016683s103,016687s104,016689s107,016697s098lbl.pdf)

PACKAGE/LABEL PRINCIPAL DISPLAY PANEL

Baxter Logo Trademark

A6C1322US

SODIUM CHLORIDE INJECTION

50

100

150

200

250ml
0.9% Sodium Chloride

[Strength] 250ml: 2.25g
[Description] This product is a clear, colorless liquid
[Dosage and Administration] Intravenous drip See the package
insert for details
For details of [Indications], [Adverse Reactions],
[Contraindications], and [Precautions], please refer to the
package insert

[Storage] Store in overwrap

The solution should be clear and should be used
up at one time
Inspect the inner bag by squeezing it and discard
solution if leakage occurs
License Number: H19994066

AA

[Drug Marketing Authorization Holder] [Manufacturer]
Name: Baxter Healthcare (Shanghai) Co., Ltd.
Address: No. 388, Tingzhu Road, Jinshan District, Shanghai

Barcode
(01)00303389791010

LOT
MFG
EXP

0.9% Sodium Chloride Injection
250ml X 40
LOT S0000000 EXP YYYY-MM
A6C1322US 1C/N LIC H19994066

0.9% Sodium Chloride Injection
250ml X 40
LOT S0000000 EXP YYYY-MM
MFG YYYY-MM-DD 1C/N 0000

Baxter Logo Trademark

A6C1323US

SODIUM CHLORIDE INJECTION

100

200

300

400

500ml
0.9% Sodium Chloride

[Strength] 500ml: 4.5g
[Description] This product is a clear, colorless liquid
[Dosage and Administration] Intravenous drip See the package
insert for details
For details of [Indications], [Adverse Reactions],
[Contraindications], and [Precautions], please refer to the
package insert

[Storage] Store in overwrap

The solution should be clear and should be used
up at one time
Inspect the inner bag by squeezing it and discard
solution if leakage occurs
License Number: H19983148

AA

[Drug Marketing Authorization Holder] [Manufacturer]
Name: Baxter Healthcare (Shanghai) Co., Ltd.
Address: No. 388, Tingzhu Road, Jinshan District, Shanghai

Barcode
(01)00303389808015

LOT
MFG
EXP

0.9% Sodium Chloride Injection
500ml X 24
LOT S0000000 EXP YYYY-MM
A6C1323US 1C/N LIC H19983148

0.9% Sodium Chloride Injection
500ml X 24
LOT S0000000 EXP YYYY-MM
MFG YYYY-MM-DD 1C/N 0000

Baxter Logo Trademark

A6C1324US

SODIUM CHLORIDE INJECTION

100

200

300

400

500

600

700

800

900

1000ml
0.9% Sodium Chloride

[Strength] 1000ml: 9g
[Description] This product is a clear, colorless liquid
[Dosage and Administration] Intravenous drip See the package
insert for details
For details of [Indications], [Adverse Reactions],
[Contraindications], and [Precautions], please refer to the
package insert

[Storage] Store in overwrap

The solution should be clear and should be used
up at one time
Inspect the inner bag by squeezing it and discard
solution if leakage occurs
License Number: H19983149

AA

[Drug Marketing Authorization Holder] [Manufacturer]
Name: Baxter Healthcare (Shanghai) Co., Ltd.
Address: No. 388, Tingzhu Road, Jinshan District, Shanghai

Barcode
(01)00303389793014

LOT
MFG
EXP

0.9% Sodium Chloride Injection
1000ml X 12
LOT S0000000 EXP YYYY-MM
A6C1324US 1C/N LIC H19983149

0.9% Sodium Chloride Injection
1000ml X 12
LOT S0000000 EXP YYYY-MM
MFG YYYY-MM-DD 1C/N 0000